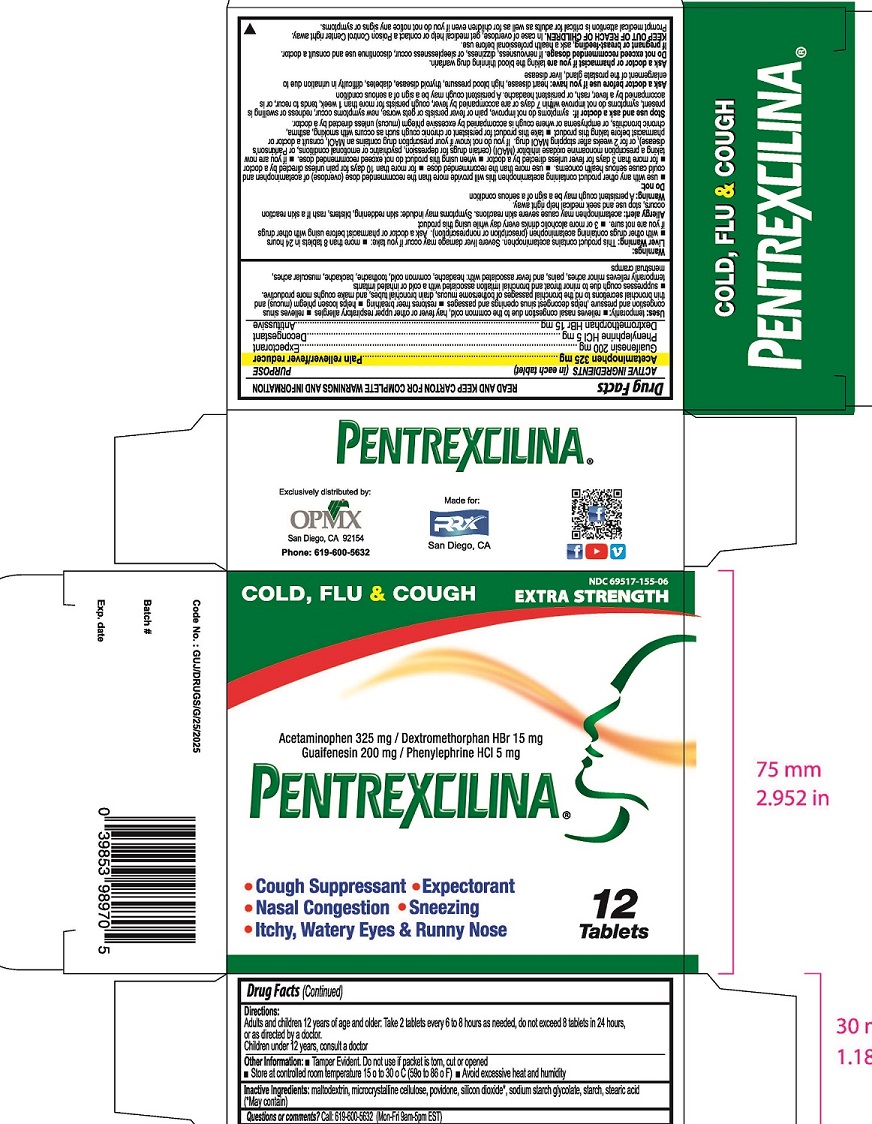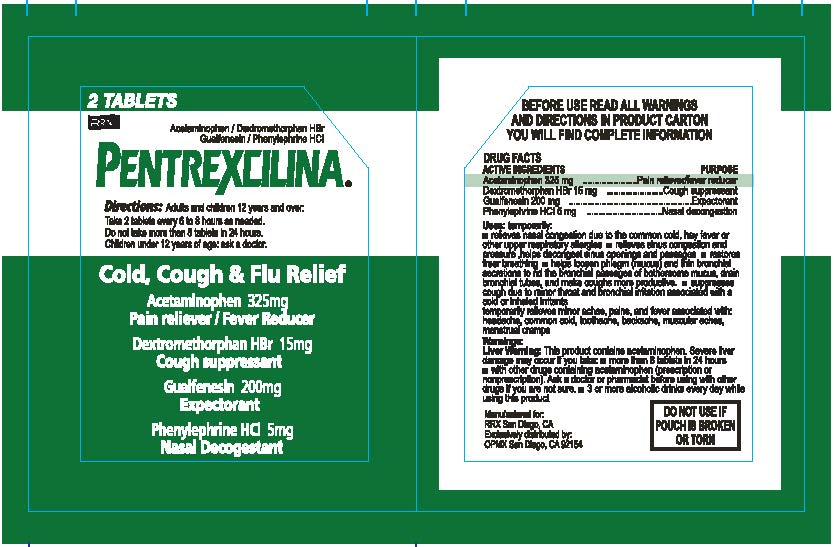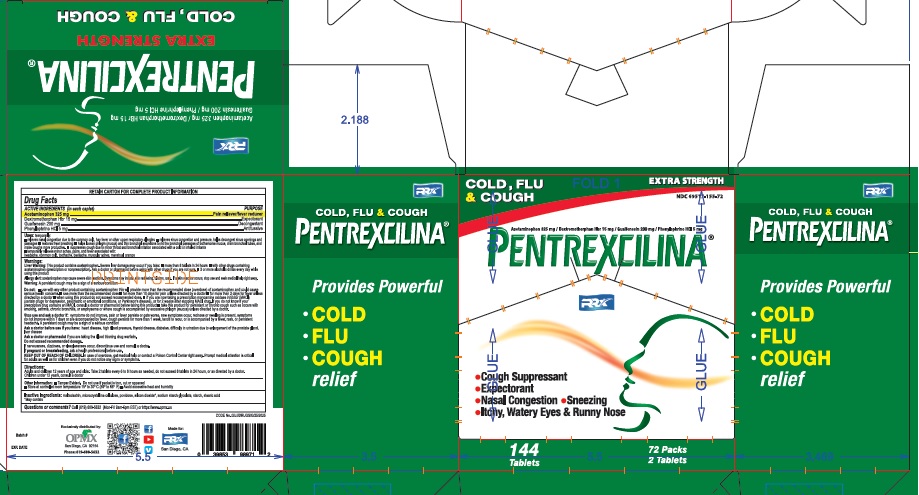 DRUG LABEL: PENTREXCILINA
NDC: 69517-155 | Form: TABLET
Manufacturer: Healthlife of USA
Category: otc | Type: HUMAN OTC DRUG LABEL
Date: 20231021

ACTIVE INGREDIENTS: ACETAMINOPHEN 325 mg/1 1; PHENYLEPHRINE HYDROCHLORIDE 5 mg/1 1; DEXTROMETHORPHAN HYDROBROMIDE 15 mg/1 1
INACTIVE INGREDIENTS: SILICON DIOXIDE; MALTODEXTRIN; CELLULOSE, MICROCRYSTALLINE; POVIDONE; STARCH, CORN; STEARIC ACID; SODIUM STARCH GLYCOLATE TYPE A CORN

PENTREXCILINA

Drug Facts

Active Ingredients (in each tablet)

Acetaminophen USP 325mg.........................................................Pain reliever/fever reducer

Guaifenesin USP 200mg..............................................................Expectorant

Phenylephrine HCL USP 5mg........................................................Decongestant

Dextromethorphan HBr USP 15mg................................................Antitussive

Purpose

Pain reliever/ fever reducer

Expectorant

Decongestant

Antitussive

Uses

Temporarily

- Relieves nasal congestion due to the common cold, hay fever or other upper respiratory allergies
- Relieves sinus congestion and pressure, helps decongest sinus openings and passages
- Restores freer breathing
- Helps loosen bothersome mucus, drain bronchial tubes, and make coughs more productive
- Suppresses cough due to minor throat and bronchial irritation associated with a cold or inhaled irritants
- Temporarily relieves minor aches, pains and fever associated with: headache, common cold, toothache, backache, muscular aches, menstrual cramps

Warnings: Liver Warning:

This product contains acetaminophen. Severe liver damage may occur if you take:

- More than 8 tablets in 24 hours
- With other drugs containing acetaminophen (prescription or nonprescription). Ask a doctor or pharmacist before using with other drugs if you are not sure
- 3 or more alcoholic drinks every day while using this product

Allergy alert:

Acetaminophen may cause severe skin reactions. Symproms may include: skin reddening, blisters, rash if a skin reaction occurs, stop use and seek medical help right away.

Warning: A persistent cough may be a sign of a serious condition

Do not

- use with any other product containing acetaminophen this will provide more than the recommended dose (overdose) of acetaminophen and cold cause serious health concerns.
- use more than the recommended dose
- for more than 10 days for pain unless directed by a doctor
- for more than 3 days for fever unless directed by a doctor
- when using this product do not exceed recommended dose
- if you are now taking a presription monoamine oxidase inhibitor (MAOI) (certain drugs for depression, psychiatric or emotional conditions, or Parkinson's disease), or for 2 weeks after stopping MAOI drug. If you do not know if your prescription drug contains an MAOI, consult a doctor or pharmacist before taking this product
- take this product for persistent or chronic cough such as occurs with smoking, asthma, chronic bronchitis, or emphysema or where cough is accompanied by excessive phlegm (mucus) unless directed by a doctor.

Stop use and ask a doctor if:

symptoms do not improve, pain or fever persists or gets worse, new symptoms occur, redness or swelling is present, symptoms do not improve within 7 days or are accompanied by fever, cough persists for more than 1 week, tends to recur, or is accompanied by a fever, rash, or persistent headache. A persistent cough may be a sign of a serious condition

Ask a doctor before use if you have:

heart disease, high blood pressure, thyroid disease, diabetes, difficulty in urination due to enlargement of the prostate gland, liver disease

Ask a doctor or pharmacist if you are

taking the blood thinning drug warfarin.

Do not exceed recommended dosage

if nervousness, dizziness, or sleeplessness occur, discontinue use consult a doctor.

If pregnant or breast-feeding,

ask a health professional before use.

KEEP OUT OF REACH OF CHILDREN

In case of overdose, get medical help or contact a Poison Control Center right away. Prompt medical attention is critical for adults as well as for children even if you do not nnotice any signs or symptoms

Directions:

Adults and children 12 years of age and older: Take 2 tablets every 6 to 8 hours as needed, do not exceed 8 tablets in 24 hours, or as directed by a doctor. Children under 12 years, consult a doctor

Other Inforamtion:

- Tamper evident. Do not use if packet is torn, cut or opened
- Store at controlled room temperature 15° to 30°C (59° to 86°F)
- Avoid excessive heat and humidity

Inactive Ingredients

maltodextrin, microcrystalline cellulose, povidone, silicon dioxide*, sodium starch glycolate, starch, stearic acid

(*may contain)

Questions or comments?

Call: 619-600-5632 (Mon-Fri 9am - 5pm EST)